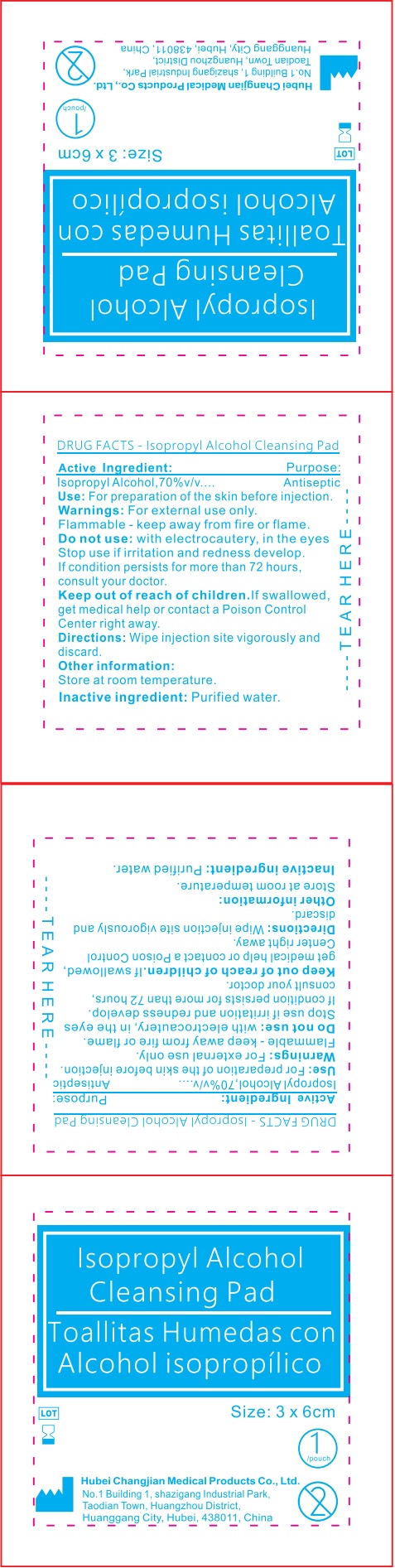 DRUG LABEL: Isopropyl Alcohol Cleansing Pad
NDC: 82996-000 | Form: CLOTH
Manufacturer: Hubei Changjian Medical Products Co., Ltd.
Category: otc | Type: HUMAN OTC DRUG LABEL
Date: 20241011

ACTIVE INGREDIENTS: ISOPROPYL ALCOHOL 700 mg/1 g
INACTIVE INGREDIENTS: WATER

Isopropyl Alcohol Cleansing Pad

Active Ingredient:

Isopropyl Alcohol,70%v/v....

Purpose:

Antiseptic

Use:

For preparation of the skin before injection.

Warnings:

For external use only.

Do not use:

with electrocautery, in the eyes Stop use if irritation and redness develop. If condition persists for more than 72 hours, consult your doctor.

Keep out of reach of children.

If swallowed, get medical help or contact a Poison Control Center right away.

Directions:

Wipe injection site vigorously and discard.

Other information:

Store at room temperature.

Inactive ingredient:

Purified water.